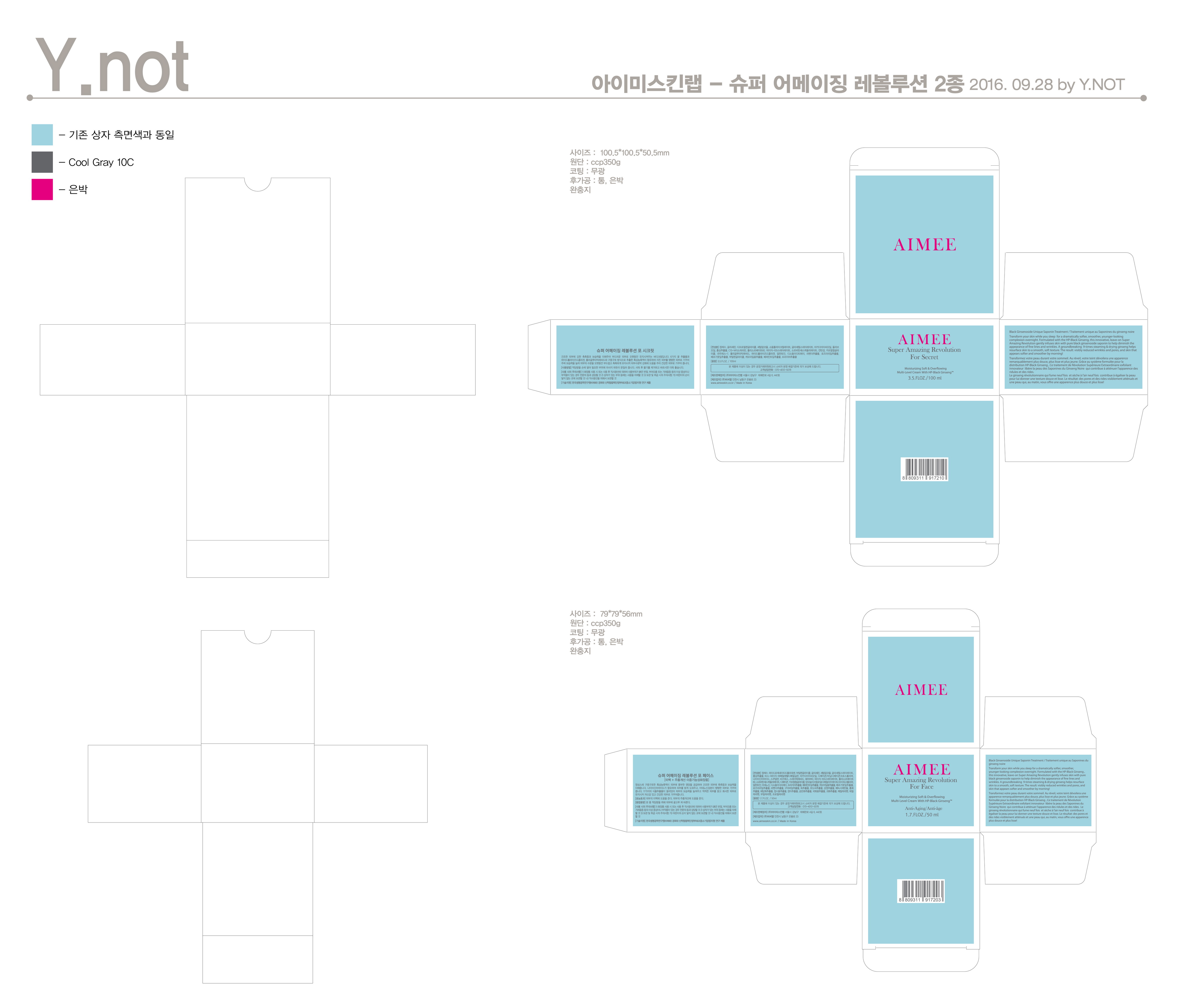 DRUG LABEL: Super Amazing Revolution For The Youth Ampoule
NDC: 71711-0005 | Form: LIQUID
Manufacturer: Aimeeskinlab Co., Ltd.
Category: otc | Type: HUMAN OTC DRUG LABEL
Date: 20211008

ACTIVE INGREDIENTS: ADENOSINE 0.05 g/100 mL
INACTIVE INGREDIENTS: GLYCERIN; WATER

Drug Facts

ACTIVE INGREDIENT

Adenosine

INACTIVE INGREDIENT

Water, Butylene Glycol, Glycerin, Panax Ginseng Root, etc.

PURPOSE

Skin Protectant - anti wrinkle, whitening

keep out of reach of the children

INDICATIONS AND USAGE

Apply a proper amount on the skin and spread evenly.

WARNINGS

For external use only.
Avoid contact with eyes. Not for human consumption.
Discontinue use if irritation occurs.
If irritation persists, consult a physician.

DOSAGE AND ADMINISTRATION

for external use only